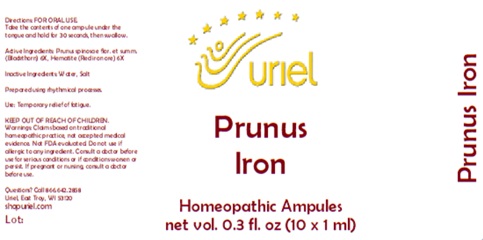 DRUG LABEL: Prunus Iron
NDC: 48951-8077 | Form: LIQUID
Manufacturer: Uriel Pharmacy Inc.
Category: homeopathic | Type: HUMAN OTC DRUG LABEL
Date: 20250122

ACTIVE INGREDIENTS: SLOE 6 [hp_X]/1 mL; FERRIC OXIDE RED 6 [hp_X]/1 mL
INACTIVE INGREDIENTS: WATER; SODIUM CHLORIDE

Prunus Iron

INDICATIONS AND USAGE

Directions: FOR ORAL USE.

DOSAGE AND ADMINISTRATION

Take the contents of one ampule under the tongue and hold for 30 seconds, then swallow.

ACTIVE INGREDIENT

Active Ingredients: Prunus spinosa e flor. et summ. (Blackthorn) 6X, Hematite (Red iron ore) 6X

Inactive Ingredients: Water, Salt

Prepared using rhythmical processes.

PURPOSE

Use: Temporary relief of fatigue.

KEEP OUT OF REACH OF CHILDREN.

WARNINGS

Warnings: Claims based on traditional homeopathic practice, not accepted medical evidence. Not FDA evaluated. Do not use if allergic to any ingredient. Consult a doctor before use for serious conditions or if conditions worsen or persist. If pregnant or nursing, consult a doctor before use.

Questions? Call 866.642.2858
Uriel, East Troy, WI 53120
shopuriel.com

Lot: